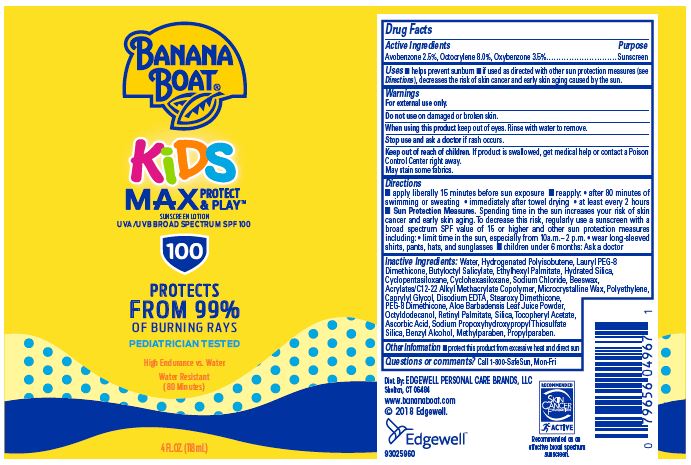 DRUG LABEL: BANANA BOAT
NDC: 63354-219 | Form: LOTION
Manufacturer: EdgewellPersonal Care Brands LLC
Category: otc | Type: HUMAN OTC DRUG LABEL
Date: 20250817

ACTIVE INGREDIENTS: OCTOCRYLENE 8 g/100 g; OXYBENZONE 3.5 g/100 g; AVOBENZONE 2.5 g/100 g
INACTIVE INGREDIENTS: HIGH DENSITY POLYETHYLENE; PROPYLPARABEN; OCTYLDODECANOL; SILICON DIOXIDE; SODIUM CHLORIDE; SODIUM PROPOXYHYDROXYPROPYL THIOSULFATE SILICA; BUTYLOCTYL SALICYLATE; ETHYLHEXYL PALMITATE; HYDRATED SILICA; CYCLOMETHICONE 5; CYCLOMETHICONE 6; BENZYL ALCOHOL; METHYLPARABEN; VITAMIN A PALMITATE; ASCORBIC ACID; WATER; MICROCRYSTALLINE WAX; CAPRYLYL GLYCOL; EDETATE DISODIUM; PEG-8 DIMETHICONE; ALOE VERA LEAF; .ALPHA.-TOCOPHEROL ACETATE

Active ingredients

Avobenzone 2.5%, Octocrylene 8.0%, Oxybenzone 3.5%

Purpose

Sunscreen

Uses

Helps prevent sunburn

If used as directed with other sun protection measures (see Directions), decreases the risk of skin cancer and early skin aging caused by the sun

Warnings

For external use only

May stain some fabrics.

Do not use

on damaged or broken skin

When using this product

Keep out of eyse. Rinse with water to remove

Stop use and ask a doctor

if rash occurs

Keep out of reach of children

If product is swallowed, get medical help or contact a Poison Control Center right away.

Directions

Apply liberally 15 minutes before sun exposure • Reapply: •after 80 minutes of swimming or sweating • immediately after towel drying • at least every 2 hours •Children under 6 months: Ask a doctor Sun Protection Measures •Spending time in the sun increases your risk of skin cancer and early skin aging. To decrease this risk, regularly use a sunscreen with a Broad Spectrum SPF value of 15 or higher and other sun protection measures including: limit time in the sun, especially from 10 a.m. - 2 p.m., wear long-sleeved shirts, pants, hats, and sunglasses.

Inactive Ingredients

Water, Hydrogenated Polyisobutene, Lauryl PEG-8 Dimethicone, Butyloctyl Salicylate,Ethylhexyl Palmitate, Hydrated Silica, Cyclopentasiloxane, Cyclohexasiloxane, Sodium Chloride, Benzyl Alcohol, Beeswax, Acrylates/C12-22 Alkyl Methacrylate Copolymer, Methylparaben, Microcrystalline Wax, Polyethylene, Caprylyl Glycol, Propylparaben,Disodium EDTA, Stearoxy Dimethicone, PEG-8 Dimethicone, Aloe Barbadensis Leaf Juice Powder, Octyldodecanol, Retinyl Palmitate, Silica, Tocopheryl Acetate, Ascorbic Acid, Sodium Propoxyhydroxypropyl Thiosulfate Silica.

Other Information

- protect this product from excessive heat and direct sun

Questions or comments?

Call 1-800-SafeSun, Mon-Fri

Principal Display Panel

BANANA
BOAT(R)
KIDS
MAX PROTECT & PLAY(TM)
SUNSCREEN LOTION
UVA/UVB BROAD SPECTRUM SPF 100
100
PROTECTS FROM 99%
OF BURNING RAYS
PEDIATRICIAN TESTED
High Endurance vs. Water
Water Resistant
(80 Minutes)
4 FL.OZ. (118 mL)